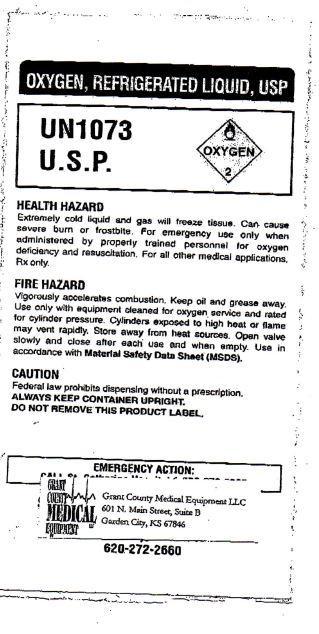 DRUG LABEL: OXYGEN
NDC: 52270-001 | Form: GAS
Manufacturer: Grant County Medical Equipment, LLC
Category: prescription | Type: HUMAN PRESCRIPTION DRUG LABEL
Date: 20140401

ACTIVE INGREDIENTS: OXYGEN 1 L/1 L

OXYGEN, REFRIGERATED LIQUID, USP